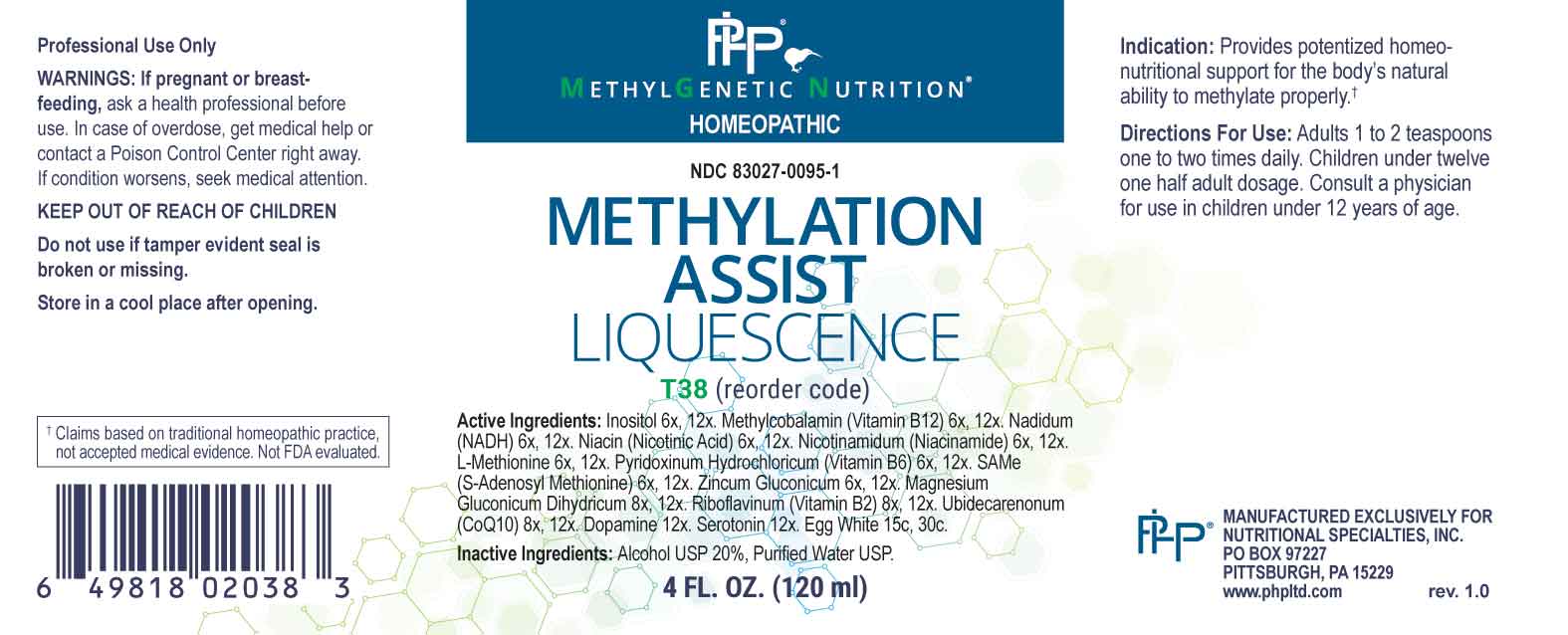 DRUG LABEL: Methylation Assist Liquescence
NDC: 83027-0095 | Form: LIQUID
Manufacturer: Nutritional Specialties, Inc.
Category: homeopathic | Type: HUMAN OTC DRUG LABEL
Date: 20230814

ACTIVE INGREDIENTS: INOSITOL 6 [hp_X]/1 mL; METHYLCOBALAMIN 6 [hp_X]/1 mL; NADIDE 6 [hp_X]/1 mL; NIACIN 6 [hp_X]/1 mL; NIACINAMIDE 6 [hp_X]/1 mL; METHIONINE 6 [hp_X]/1 mL; PYRIDOXINE HYDROCHLORIDE 6 [hp_X]/1 mL; ADEMETIONINE 6 [hp_X]/1 mL; ZINC GLUCONATE 6 [hp_X]/1 mL; MAGNESIUM GLUCONATE 8 [hp_X]/1 mL; RIBOFLAVIN 8 [hp_X]/1 mL; UBIDECARENONE 8 [hp_X]/1 mL; DOPAMINE HYDROCHLORIDE 12 [hp_X]/1 mL; SEROTONIN HYDROCHLORIDE 12 [hp_X]/1 mL; EGG WHITE 15 [hp_C]/1 mL
INACTIVE INGREDIENTS: WATER; ALCOHOL

DRUG FACTS:

ACTIVE INGREDIENTS:

Inositol 6X, 12X, Methylcobalamin (Vitamin B12) 6X, 12X, Nadidum (NADH) 6X, 12X, Niacin (Nicotinic Acid) 6X, 12X, Nicotinamidum (Niacinamide) 6X, 12X, L-Methionine 6X, 12X, Pyridoxinum Hydrochloricum (Vitamin B6) 6X, 12X, SAMe (S-Adenosyl Methionine) 6X, 12X, Zincum Gluconicum 6X, 12X, Magnesium Gluconicum Dihydricum 8X, 12X, Riboflavinum (Vitamin B2) 8X, 12X, Ubidecarenonum CoQ10) 8X, 12X, Dopamine 12X, Serotonin 12X, Egg White 15C, 30C.

PURPOSE:

Provides potentized homeo-nutritional support for the body's natural ability to methylate properly.†

†Claims based on traditional homeopathic practice, not accepted medical evidence. Not FDA evaluated.

WARNINGS:

Professional Use Only

If pregnant or breast-feeding, ask a health professional before use.

In case of overdose, get medical help or contact a Poison Control Center right away.

If condition worsens, seek medical attention.

KEEP OUT OF REACH OF CHILDREN

Do not use if tamper evident seal is broken or missing.

Store in a cool place after opening

KEEP OUT OF REACH OF CHILDREN:

In case of overdose, get medical help or contact a Poison Control Center right away.

DIRECTIONS:

Adults 1 to 2 teaspoons one to two times daily. Children under twelve one half adult dosage. Consult a physician for use in children under 12 years of age.

INDICATIONS:

Provides potentized homeo-nutritional support for the body's natural ability to methylate properly.†

†Claims based on traditional homeopathic practice, not accepted medical evidence. Not FDA evaluated.

INACTIVE INGREDIENTS:

Alcohol USP 20%, Purified Water USP.

QUESTIONS:

MANUFACTURED EXCLUSIVELY FOR

NUTRITIONAL SPECIALTIES, INC.

PO BOX 97227

PITTSBURG, PA 15229

www.phpltd.com

PACKAGE LABEL DISPLAY:

METHYLGENETIC NUTRITION

HOMEOPATHIC

NDC 83027-0095-1

METHYLATION

ASSIST

LIQUESCENCE

4 FL. OZ (120 ml)